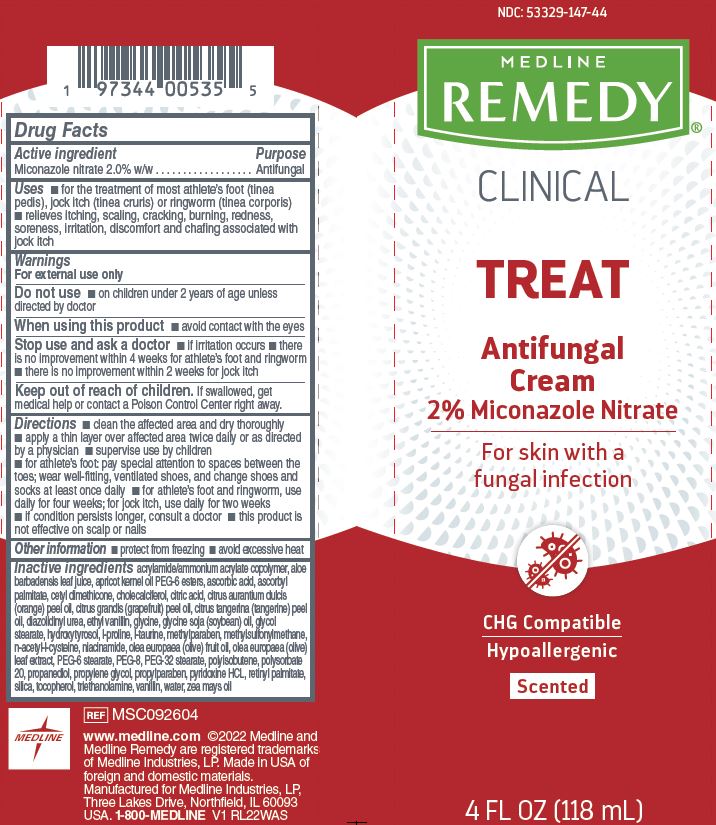 DRUG LABEL: Medline
NDC: 53329-147 | Form: CREAM
Manufacturer: Medline Industries, LP
Category: otc | Type: HUMAN OTC DRUG LABEL
Date: 20251024

ACTIVE INGREDIENTS: MICONAZOLE NITRATE 20 mg/1 mL
INACTIVE INGREDIENTS: GLYCINE; PYRIDOXINE HYDROCHLORIDE; GLYCOL STEARATE; OLIVE OIL; POLYSORBATE 20; METHYLPARABEN; DIMETHYL SULFONE; NIACINAMIDE; CITRUS MAXIMA FRUIT RIND OIL; TOCOPHEROL; CHOLECALCIFEROL; ASCORBYL PALMITATE; PROPANEDIOL; APRICOT KERNEL OIL PEG-6 ESTERS; SOYBEAN OIL; POLYISOBUTYLENE (1000 MW); SORBITAN ISOSTEARATE; PROPYLENE GLYCOL; DIAZOLIDINYL UREA; PROPYLPARABEN; SILICON DIOXIDE; CETYL DIMETHICONE 150; WATER; VITAMIN A PALMITATE; ACETYLCYSTEINE; PEG-32 STEARATE; CITRIC ACID MONOHYDRATE; PROLINE; ETHYL VANILLIN; ALOE VERA LEAF; POLYETHYLENE GLYCOL 400; PEG-6 STEARATE; TROLAMINE; TAURINE; ORANGE OIL; MANDARIN OIL; ASCORBIC ACID; HYDROXYTYROSOL; CORN OIL

147 Remedy Clinical Antifungal Cream

Active ingredient

Miconazole nitrate 2.0% w/w

Purpose

Antifungal

Uses

- for the treatment of most athlete’s foot (tinea pedis), jock itch (tinea cruris) or ringworm (tinea corporis)
- relieves itching, scaling, cracking, burning, redness, soreness, irritation, discomfort and chafing associated with jock itch

Warnings

For external use only

Do not use

- on children under 2 years of age unless directed by doctor

When using this product

- avoid contact with the eyes

Stop use and ask a doctor

- if irritation occurs
- there is no improvement within 4 weeks for athlete’s foot and ringworm
- there is no improvement within 2 weeks for jock itch

Keep out of reach of children.

If swallowed, get medical help or contact a Poison Control Center right away.

Directions

- clean the affected area and dry thoroughly
- apply a thin layer over affected area twice daily or as directed by a physician
- supervise use by children
- for athlete’s foot: pay special attention to spaces between the toes; wear well-fitting, ventilated shoes, and change shoes and socks at least once daily
- for athlete’s foot and ringworm, use daily for four weeks; for jock itch, use daily for two weeks
- if condition persists longer, consult a doctor
- this product is not effective on scalp or nails

Other information

- protect from freezing
- avoid excessive heat

Inactive ingredients

acrylamide/ammonium acrylate copolymer, aloe barbadensis leaf juice, apricot kernel oil PEG-6 esters, ascorbic acid, ascorbyl palmitate, cetyl dimethicone, cholecalciferol, citric acid, citrus aurantium dulcis (orange) peel oil, citrus grandis (grapefruit) peel oil, citrus tangerina (tangerine) peel oil, diazolidinyl urea, ethyl vanillin, glycine, glycine soja (soybean) oil, glycol stearate, hydroxytyrosol, l-proline, l-taurine, methylparaben, methylsulfonylmethane, n-acetyl-l-cysteine, niacinamide, olea europaea (olive) fruit oil, olea europaea (olive) leaf extract, PEG-6 stearate, PEG-8, PEG-32 stearate, polyisobutene, polysorbate 20, propanediol, propylene glycol, propylparaben, pyridoxine HCL, retinyl palmitate, silica, tocopherol, triethanolamine, vanillin, water, zea mays oil

Manufacturing Information

www.medline.com

©2022 Medline and Medline Remedy

are registered trademarks of

Medline Industries, LP.

Made in USA of foreign and domestic materials

Manufactured for Medline Industries, LP,

Three Lakes Drive, Northfield, IL 60093 USA

1-800-MEDLINE

REF: MSC092604